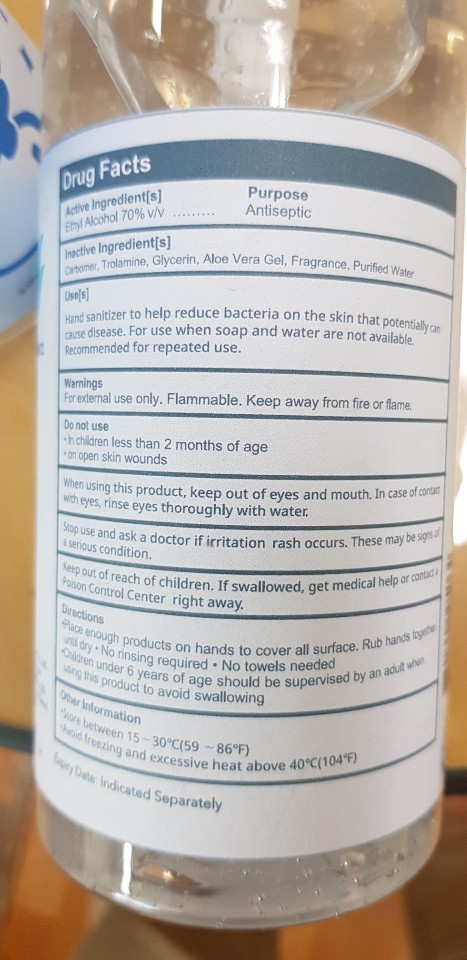 DRUG LABEL: SORU
NDC: 78425-0005 | Form: GEL
Manufacturer: GS CHEM CO LTD
Category: otc | Type: HUMAN OTC DRUG LABEL
Date: 20200626

ACTIVE INGREDIENTS: ALCOHOL 70 mL/100 mL
INACTIVE INGREDIENTS: GLYCERIN; WATER; CARBOMER 940; TROLAMINE; ALOE VERA LEAF

ACTIVE INGREDIENT

alcohol

INACTIVE INGREDIENT

WATER
CARBOMER
GLYCERIN
TRIETHANOLAMINE

aloe vera gel

fragrance

PURPOSE

for hand-washing to decrease bacteria on the skin, only when water is not available

Keep out of reach of children

INDICATIONS AND USAGE

wet hands thoroughly with product and allow to dry without wiping

WARNINGS

Flammable, keep away from fire and flames
Fot external use only.

DOSAGE AND ADMINISTRATION

For external use only